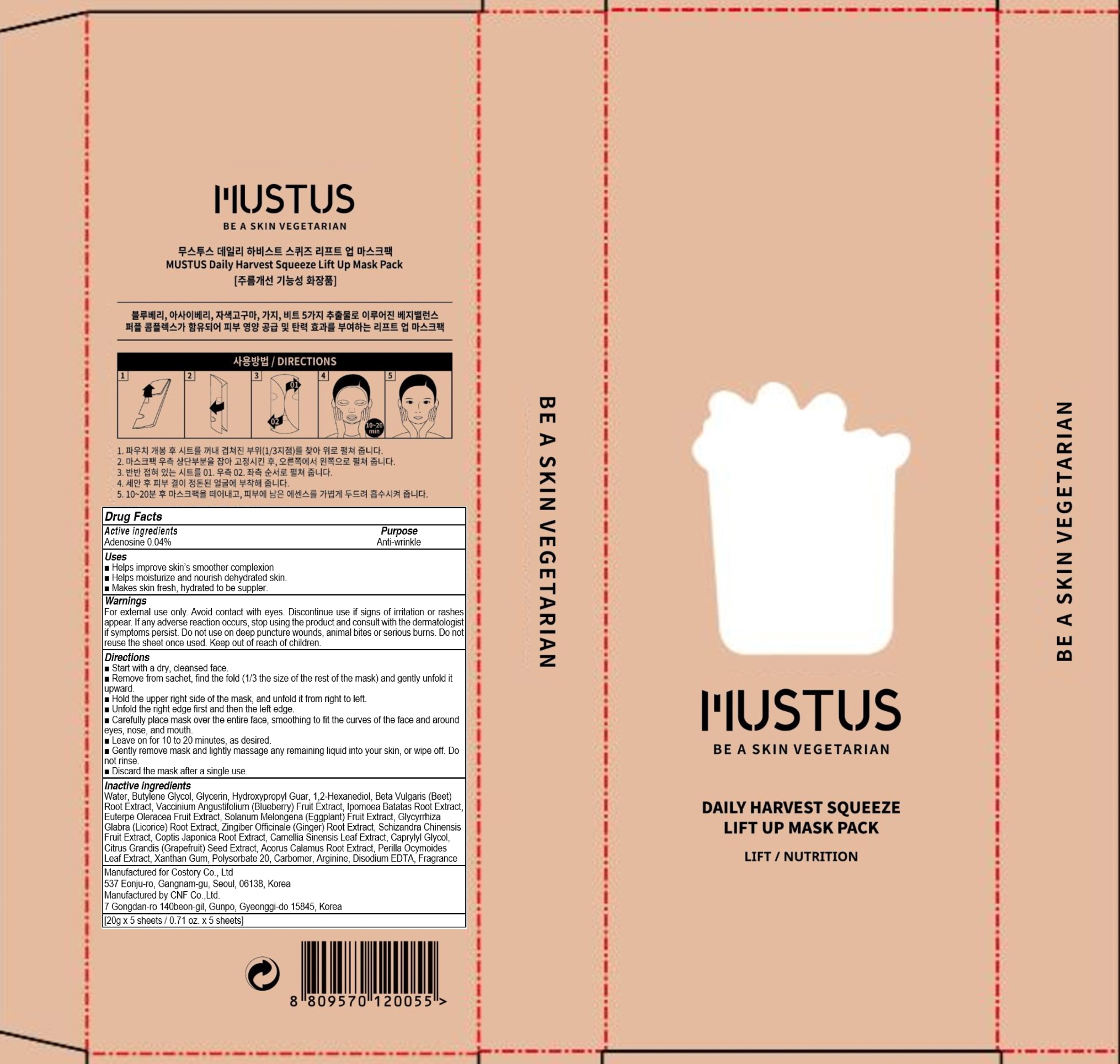 DRUG LABEL: MUSTUS DAILY HARVEST SQUEEZE LIFT UP MASK PACK
NDC: 73020-020 | Form: PATCH
Manufacturer: Costory Co., Ltd
Category: otc | Type: HUMAN OTC DRUG LABEL
Date: 20190503

ACTIVE INGREDIENTS: Adenosine 0.008 g/20 g
INACTIVE INGREDIENTS: Water; Butylene Glycol

<br>

ACTIVE INGREDIENT

Active ingredients: Adenosine 0.04%

INACTIVE INGREDIENT

Inactive ingredients:
Water, Butylene Glycol, Glycerin, Hydroxypropyl Guar, 1,2-Hexanediol, Beta Vulgaris (Beet) Root Extract, Vaccinium Angustifolium (Blueberry) Fruit Extract, Ipomoea Batatas Root Extract, Euterpe Oleracea Fruit Extract, Solanum Melongena (Eggplant) Fruit Extract, Glycyrrhiza Glabra (Licorice) Root Extract, Zingiber Officinale (Ginger) Root Extract, Schizandra Chinensis Fruit Extract, Coptis Japonica Root Extract, Camellia Sinensis Leaf Extract, Caprylyl Glycol, Citrus Grandis (Grapefruit) Seed Extract, Acorus Calamus Root Extract, Perilla Ocymoides Leaf Extract, Xanthan Gum, Polysorbate 20, Carbomer, Arginine, Disodium EDTA, Fragrance

PURPOSE

Purpose: Anti-wrinkle

WARNINGS

For external use only. Avoid contact with eyes. Discontinue use if signs of irritation or rashes appear. If any adverse reaction occurs, stop using the product and consult with the dermatologist if symptoms persist. Do not use on deep puncture wounds, animal bites or serious burns. Do not reuse the sheet once used. Keep out of reach of children.

KEEP OUT OF REACH OF CHILDREN

Uses

■ Helps improve skin’s smoother complexion
■ Helps moisturize and nourish dehydrated skin.
■ Makes skin fresh, hydrated to be suppler.

Directions

■ Start with a dry, cleansed face.
■ Remove from sachet, find the fold(1/3 the size of the rest of the mask) and gently unfold it upward.
■ Hold the upper right side of the mask, and unfold it from right to left.
■ Unfold the right edge first and then the left edge.
■ Carefully place mask over the entire face, smoothing to fit the curves of the face and around eyes, nose, and mouth.
■ Leave on for 10 to 20 minutes, as desired.
■ Gently remove mask and lightly massage any remaining liquid into your skin, or wipe off. Do not rinse.
■ Discard the mask after a single use.